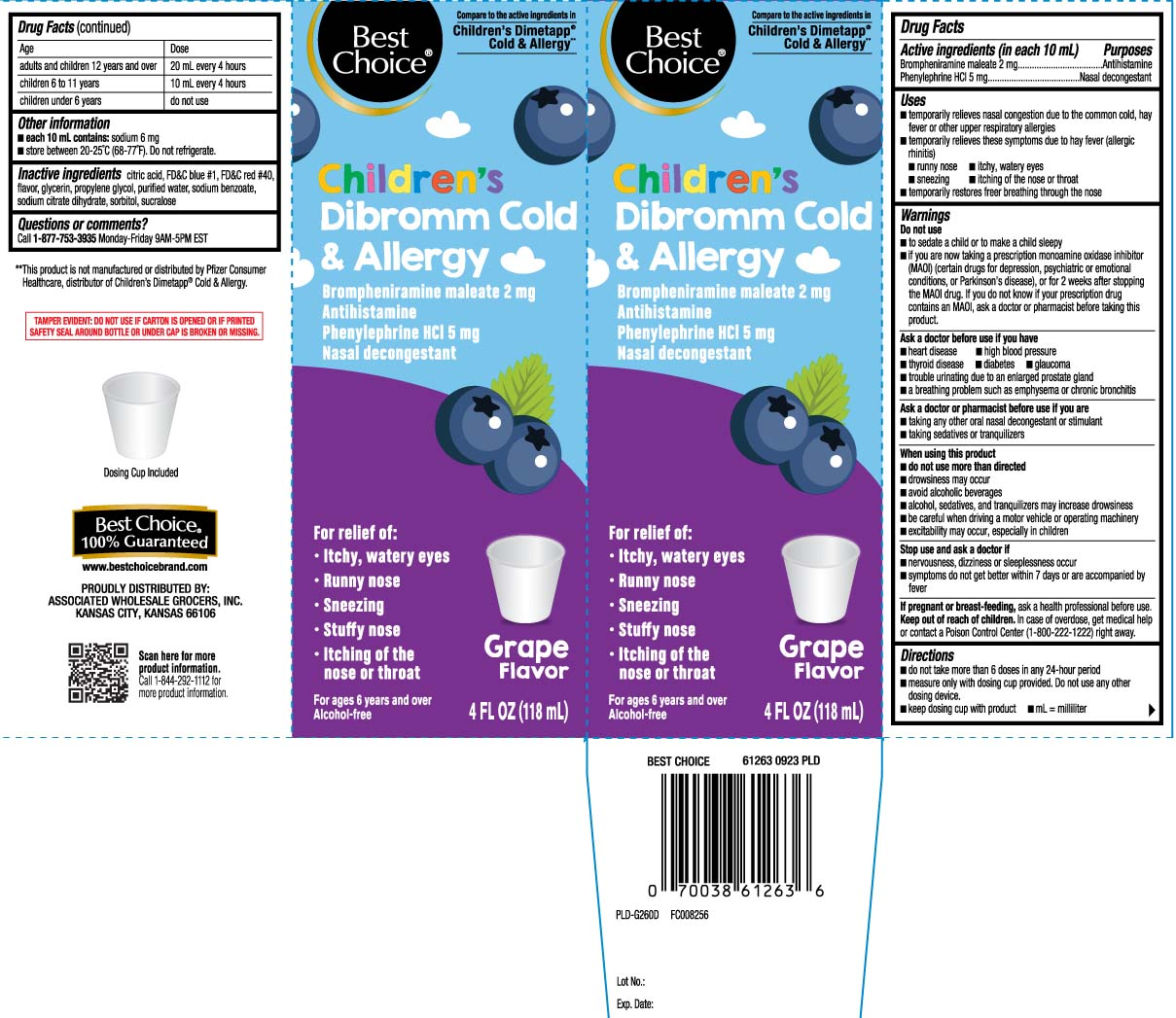 DRUG LABEL: Childrens Cold and Allergy
NDC: 63941-012 | Form: LIQUID
Manufacturer: Best Choice  (Valu Merchandisers Company)
Category: otc | Type: HUMAN OTC DRUG LABEL
Date: 20260224

ACTIVE INGREDIENTS: BROMPHENIRAMINE MALEATE 2 mg/10 mL; PHENYLEPHRINE HYDROCHLORIDE 5 mg/10 mL
INACTIVE INGREDIENTS: FD&C BLUE NO. 1; FD&C RED NO. 40; GLYCERIN; PROPYLENE GLYCOL; WATER; SODIUM BENZOATE; TRISODIUM CITRATE DIHYDRATE; SORBITOL; SUCRALOSE; ANHYDROUS CITRIC ACID

Drug Facts

Active ingredients (in each 10 mL)

Brompheniramine maleate 2 mg

Phenylephrine HCI 5 mg

Purposes

Antihistamine

Nasal decongestant

Uses

- temporarily relieves nasal congestion due to the common cold, hay fever or other upper respiratory allergies
- temporarily relieves these symptoms due to hay fever (allergic rhinitis)
  - runny nose
  - itchy, watery eyes
  - sneezing
  - itching of the nose or throat
- temporarily restores freer breathing through the nose

Warnings

Do not use

- to sedate a child or to make a child sleepy
- if you are now taking a prescription monoamine oxidase inhibitor (MAOI) (certain drugs for depression, psychiatric or emotional conditions, or Parkinson's disease), or for 2 weeks after stopping the MAOI drug. If you do not know if your prescription drug contains an MAOI, ask a doctor or pharmacist before taking this product.

Ask a doctor before use if you have

- heart disease
- high blood pressure
- thyroid disease
- diabetes
- glaucoma
- trouble urinating due to an enlarged prostate gland
- a breathing problem such as emphysema or chronic bronchitis

Ask a doctor or pharmacist before use if you are

- taking any other oral nasal decongestant or stimulant
- taking sedatives or tranquilizers

When using this product

- do not use more than directed
- drowsiness may occur
- avoid alcoholic beverages
- alcohol, sedatives, and tranquilizers may increase drowsiness
- be careful when driving a motor vehicle or operating machinery
- excitability may occur, especially in children

Stop use and ask a doctor if

- nervousness, dizziness or sleeplessness occur
- symptoms do not get better within 7 days or are accompanied by fever

If pregnant or breast-feeding,

ask a health professional before use.

Keep out of reach of children.

In case of overdose, get medical help or contact a Poison Control Center (1-800-222-1222) right away.

Directions

- do not take more than 6 doses in any 24-hour period
- measure only with dosing cup provided. Do not use any other dosing device.
- keep dosing cup with product
- mL = milliliter

age | dose
adults and children 12 years and over | 20 mL every 4 hours
children 6 to 11 years | 10 mL every 4 hours
children under 6 years | do not use

Other information

- each 10 mL contains: sodium 6 mg
- store between 20-25°C (68-77°F). Do not refrigerate.

Inactive ingredients

anhydrous citric acid, FD&C blue #1, FD&C red # 40, flavor, glycerin, propylene glycol, purified water, sodium benzoate, sorbitol, sucralose, trisodium citrate dihydrate

Questions or comments?

Call 1-877-753-3935 Monday-Friday 9AM-5PM EST

Principal Display Panel

Compare to the active ingredients in Childreb's Dimetapp® Cold & Allergy**

Children's

Dibromm Cold & Allergy

Brompheniramine maleate 2 mg

Antihistamine

Phenylephrine HCl 5 mg

Nasal decongestant

For relief of:

- Itchy, watery eyes
- Runny Nose
- Sneezing
- Stuffy nose
- Itching of the nose or throat

For ages 6 years and over

Alcohol-free

Grape Flavor

Dosing Cup Included

FL OZ (mL)

**This product is not manufactured or distributed by Pfizer Consumer Healthcare, distributors of Children's Dimetapp® Cold & Allergy.

TAMPER EVIDENT: DO NOT USE IF CARTON IS OPENED OR IF PRINTED SAFETY SEAL AROUND BOTTLE OR UNDER CAP IS BROKEN OR MISSING.

PROUDLY DISTRIBUTED BY:

ASSOCIATED WHOLESALE GROCERS, INC.

KANSAS CITY, KANSAS 66106

Package Label

BEST CHOICE Children's Cold & Allergy